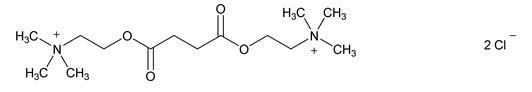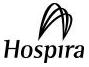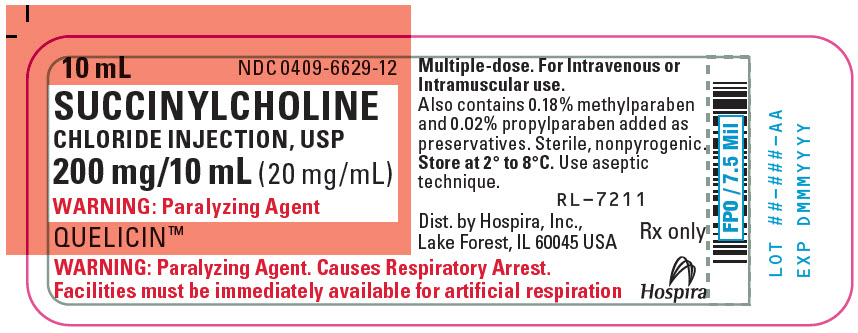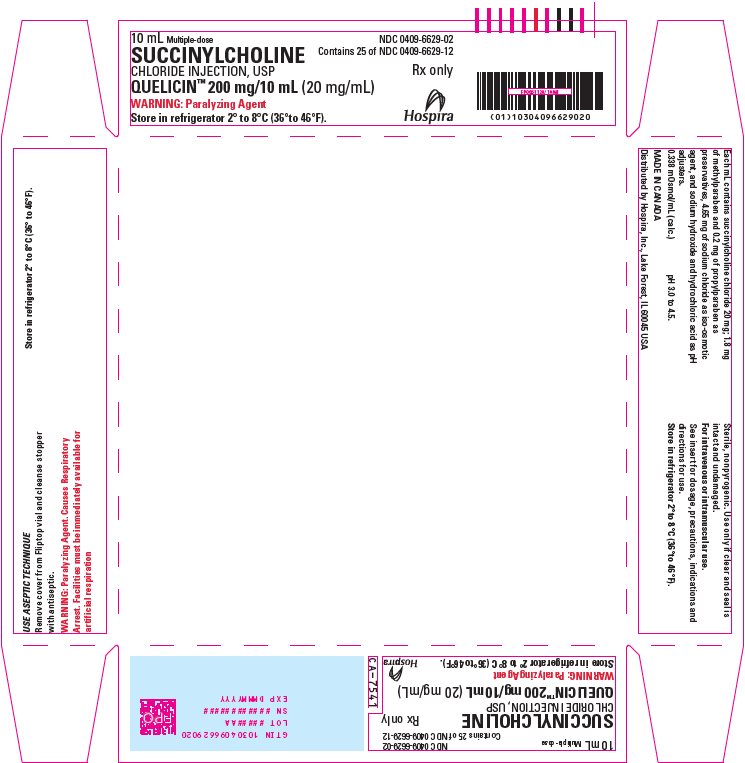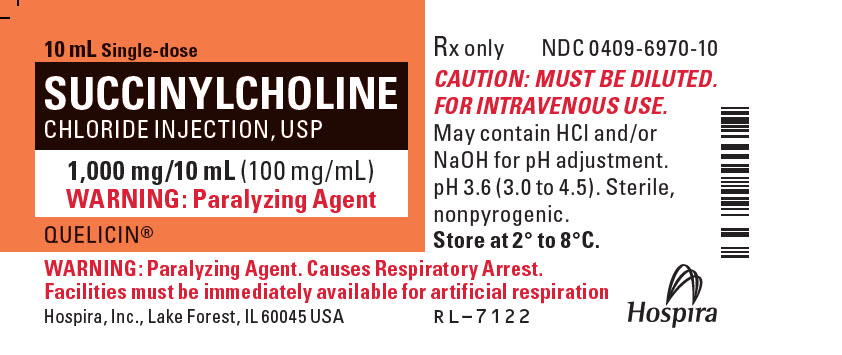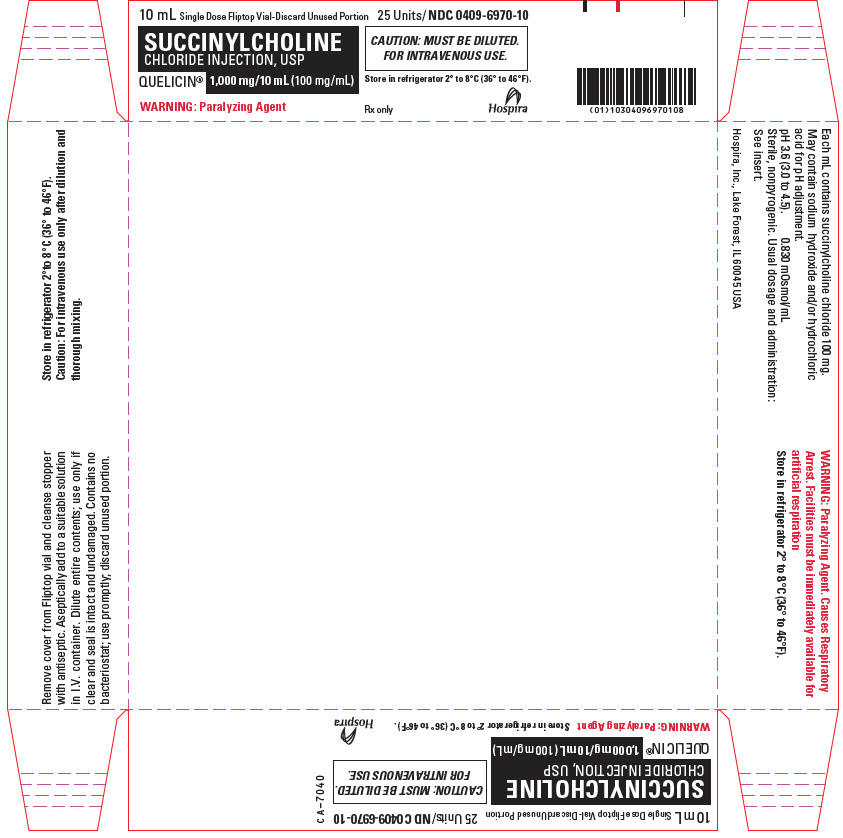 DRUG LABEL: QUELICIN
NDC: 0409-6629 | Form: INJECTION, SOLUTION
Manufacturer: Hospira, Inc.
Category: prescription | Type: HUMAN PRESCRIPTION DRUG LABEL
Date: 20241226

ACTIVE INGREDIENTS: SUCCINYLCHOLINE CHLORIDE 20 mg/1 mL
INACTIVE INGREDIENTS: SODIUM HYDROXIDE; HYDROCHLORIC ACID; SODIUM CHLORIDE; METHYLPARABEN 1.8 mg/1 mL; PROPYLPARABEN 0.2 mg/1 mL

HIGHLIGHTS OF PRESCRIBING INFORMATION

These highlights do not include all the information needed to use QUELICIN™ safely and effectively. See full prescribing information for QUELICIN™.
QUELICIN™ (succinylcholine chloride) injection, for intravenous or intramuscular use
Initial U.S. Approval: 1952

WARNING: VENTRICULAR DYSRHYTHMIAS, CARDIAC ARREST, AND DEATH FROM HYPERKALEMIC RHABDOMYOLYSIS IN PEDIATRIC PATIENTS

See full prescribing information for complete boxed warning.

- Acute rhabdomyolysis with hyperkalemia followed by ventricular dysrhythmias, cardiac arrest, and death has occurred after use in apparently healthy pediatric patients who were subsequently found to have undiagnosed skeletal muscle myopathy. (5.1)
- When a healthy-appearing pediatric patient develops cardiac arrest soon after administration of QUELICIN, not felt to be due to other causes, immediate treatment for hyperkalemia should be instituted. In the presence of signs of malignant hyperthermia, appropriate treatment should be instituted concurrently. (5.1)
- Reserve use of QUELICIN in pediatric patients for emergency intubation or instances where immediate securing of the airway is necessary, or for intramuscular use when a suitable vein is inaccessible. (5.1)

RECENT MAJOR CHANGES

Contraindications (4) | 11/2022
Warnings and Precautions, Malignant Hyperthermia (5.5) | 11/2022

1 INDICATIONS AND USAGE

QUELICIN is a depolarizing neuromuscular blocker indicated in adults and pediatric patients:

- as an adjunct to general anesthesia (1)
- to facilitate tracheal intubation (1)
- to provide skeletal muscle relaxation during surgery or mechanical ventilation. (1)

2 DOSAGE AND ADMINISTRATION

- For intravenous or intramuscular use only. (2.1)
- Individualize dosage after careful assessment of the patient. (2.1)
- Accidental administration of neuromuscular blocking agents may be fatal. Store QUELICIN with the cap and ferrule intact and in a manner that minimizes the possibility of selecting the wrong product. (2.1)
- See full prescribing information for QUELICIN dosage recommendations, preparation instructions, and administration information. (2.2, 2.3, 2.4, 2.5, 2.6)

3 DOSAGE FORMS AND STRENGTHS

Injection:

- 1,000 mg/10 mL (100 mg/mL) in single-dose fliptop vials (3)
- 200 mg/10 mL (20 mg/mL) in multiple-dose fliptop vials (3)

4 CONTRAINDICATIONS

- Skeletal muscle myopathies (4)
- Known hypersensitivity to succinylcholine (4)
- After the acute phase of injury following major burns, multiple trauma, extensive denervation of skeletal muscle, or upper motor neuron injury (4)
- Known or suspected genetic susceptibility to malignant hyperthermia (4)

5 WARNINGS AND PRECAUTIONS

- Anaphylaxis: Severe anaphylactic reactions to neuromuscular blocking agents, including succinylcholine, have been reported. Some cases have been life-threatening and fatal. Take necessary precautions, such as the immediate availability of appropriate emergency treatment. (5.2)
- Risk of Death due to Medication Errors: Unintended administration of QUELICIN may result in paralysis, respiratory arrest and death. Confirm proper selection of intended product and avoid confusion with other injectable solutions that are present in critical care and other clinical settings. (5.3)
- Hyperkalemia: QUELICIN may induce serious cardiac arrhythmias or cardiac arrest due to hyperkalemia. (5.4)
- Malignant Hyperthermia: Malignant hyperthermia may occur, especially in individuals with known or suspected susceptibility based on genetic factors or family history. Discontinue triggering agents, administer intravenous dantrolene sodium, and apply supportive therapies. (5.5)
- Bradycardia: Intravenous bolus administration may result in profound bradycardia or, rarely, asystole. The incidence is higher following a second dose of succinylcholine. Pretreatment with anticholinergic agents (e.g., atropine) may reduce the occurrence of bradyarrhythmias. (5.6)

6 ADVERSE REACTIONS

Adverse reactions reported with succinylcholine are cardiac arrest, malignant hyperthermia, arrhythmias, bradycardia, tachycardia, hypertension, hypotension, hyperkalemia, prolonged respiratory depression or apnea. (6)
To report SUSPECTED ADVERSE REACTIONS, contact Pfizer, Inc. at 1-800-438-1985 or FDA at 1-800-FDA-1088 or www.fda.gov/medwatch.

7 DRUG INTERACTIONS

Drugs that May Enhance the Neuromuscular Blocking Action of Succinylcholine: promazine, oxytocin, aprotinin, certain non-penicillin antibiotics, quinidine, β-adrenergic blockers, procainamide, lidocaine, trimethaphan, lithium carbonate, magnesium salts, quinine, chloroquine, isoflurane, desflurane, metoclopramide, terbutaline, and drugs that reduce plasma cholinesterase activity. (7.1)

FULL PRESCRIBING INFORMATION

WARNING: VENTRICULAR DYSRHYTHMIAS, CARDIAC ARREST, AND DEATH FROM HYPERKALEMIC RHABDOMYOLYSIS IN PEDIATRIC PATIENTS

- Acute rhabdomyolysis with hyperkalemia followed by ventricular dysrhythmias, cardiac arrest, and death has occurred after the administration of succinylcholine to apparently healthy pediatric patients who were subsequently found to have undiagnosed skeletal muscle myopathy, most frequently Duchenne muscular dystrophy [see Warnings and Precautions (5.1)].
- When a healthy appearing pediatric patient develops cardiac arrest within minutes after administration of QUELICIN, not felt to be due to inadequate ventilation, oxygenation or anesthetic overdose, immediate treatment for hyperkalemia should be instituted. In the presence of signs of malignant hyperthermia, appropriate treatment should be instituted concurrently [see Warnings and Precautions (5.1)].
- Reserve the use of QUELICIN in pediatric patients for emergency intubation or instances where immediate securing of the airway is necessary, e.g., laryngospasm, difficult airway, full stomach, or for intramuscular use when a suitable vein is inaccessible [see Warnings and Precautions (5.1)].

1 INDICATIONS AND USAGE

QUELICIN is indicated in adults and pediatric patients:

- as an adjunct to general anesthesia
- to facilitate tracheal intubation
- to provide skeletal muscle relaxation during surgery or mechanical ventilation.

2 DOSAGE AND ADMINISTRATION

2.1 Important Dosage and Administration Information

- QUELICIN is for intravenous or intramuscular use only.
- QUELICIN must be titrated to effect by or under supervision of experienced clinicians who are familiar with its actions and with appropriate neuromuscular monitoring techniques.
- QUELICIN should be administered only by those skilled in the management of artificial respiration and only when facilities are instantly available for tracheal intubation and for providing adequate ventilation of the patient, including the administration of oxygen under positive pressure and the elimination of CO2. The clinician must be prepared to assist or control respiration.
- The dosage of QUELICIN should be individualized and should always be determined by the clinician after careful assessment of the patient.
- To avoid distress to the patient, do not administer QUELICIN before unconsciousness has been induced [see Warnings and Precautions (5.14)].
- The occurrence of bradyarrhythmias with administration of QUELICIN may be reduced by pretreatment with anticholinergics (e.g., atropine) [see Warnings and Precautions (5.6)].
- Monitor neuromuscular function with a peripheral nerve stimulator when using QUELICIN by infusion [see Dosage and Administration (2.2), Warnings and Precautions (5.8)].
- Visually inspect QUELICIN for particulate matter and discoloration prior to administration, whenever solution and container permit. Do not administer solutions that are not clear and colorless.
- QUELICIN supplied in single-dose vials must be diluted before use. QUELICIN supplied in multiple-dose vials does not require dilution before use [see Dosage and Administration (2.5)].

Risk of Medication Errors

Accidental administration of neuromuscular blocking agents may be fatal. Store QUELICIN with the cap and ferrule intact and in a manner that minimizes the possibility of selecting the wrong product [see Warnings and Precautions (5.3)].

2.2 Dosage Recommendations for Intravenous Use in Adults

For Short Surgical Procedures

The average dose required to produce neuromuscular blockade and to facilitate tracheal intubation is 0.6 mg/kg QUELICIN given intravenously. The optimum intravenous dose of QUELICIN will vary among patients and may be from 0.3 mg/kg to 1.1 mg/kg for adults. Following intravenous administration of doses in this range, neuromuscular blockade develops in about 1 minute; maximum blockade may persist for about 2 minutes, after which recovery takes place within 4 to 6 minutes. A 5 to 10 mg intravenous test dose of QUELICIN may be used to determine the sensitivity of the patient and the individual recovery time [see Warnings and Precautions (5.9)].

For Long Surgical Procedures

Continuous Intravenous Infusion

The dosage of QUELICIN administered by continuous intravenous infusion depends upon the duration of the surgical procedure and the need for muscle relaxation.

Diluted QUELICIN solutions containing from 1 mg/mL to 2 mg/mL succinylcholine have commonly been used for continuous intravenous infusion [see Dosage and Administration (2.5)]. The more dilute solution (1 mg/mL) is probably preferable from the standpoint of ease of control of the rate of administration of QUELICIN and, hence, of relaxation. This diluted QUELICIN solution containing 1 mg/mL succinylcholine may be administered intravenously at a rate of 0.5 mg (0.5 mL) per minute to 10 mg (10 mL) per minute to obtain the required amount of relaxation. The amount required per minute will depend upon the individual response as well as the degree of relaxation required. The average rate of continuous intravenous infusion for an adult ranges between 2.5 mg per minute and 4.3 mg per minute.

Monitor neuromuscular function with a peripheral nerve stimulator when using QUELICIN by infusion in order to avoid overdose, detect development of Phase II block, follow its rate of recovery, and assess the effects of reversing agents [see Warnings and Precautions (5.8)].

Intermittent Intravenous Injection

Intermittent intravenous injections of QUELICIN may also be used to provide muscle relaxation for long procedures. An intravenous injection of 0.3 mg/kg to 1.1 mg/kg may be given initially, followed, at appropriate intervals, by further intravenous injections of 0.04 mg/kg to 0.07 mg/kg to maintain the degree of relaxation required.

2.3 Dosage Recommendations for Intravenous Use in Pediatric Patients

For emergency tracheal intubation or in instances where immediate securing of the airway is necessary, the intravenous dose of QUELICIN is 2 mg/kg for infants and other small pediatric patients; for older pediatric patients and adolescents the intravenous dose is 1 mg/kg [see Warnings and Precautions (5.1), Use in Specific Populations (8.4)]. The effective dose of QUELICIN in pediatric patients may be higher than that predicted by body weight dosing alone. For example, the usual adult intravenous dose of 0.6 mg/kg is comparable to a dose of 2 mg/kg to 3 mg/kg in neonates and infants up to 6 months of age and 1 mg/kg to 2 mg/kg in infants up to 2 years of age [see Clinical Pharmacology (12.3)].

2.4 Dosage Recommendations for Intramuscular Use in Adults and Pediatric Patients

If a suitable vein is inaccessible, QUELICIN may be administered intramuscularly at a dose of up to 3 mg/kg to 4 mg/kg to infants, older pediatric patients, or adults. The total dose administered by the intramuscular route should not exceed 150 mg. The onset of effect of succinylcholine given intramuscularly is usually observed in about 2 to 3 minutes.

2.5 Preparation of QUELICIN

QUELICIN supplied in single-dose vials must be diluted before use. QUELICIN supplied in multiple-dose vials does not require dilution before use.

QUELICIN may be diluted to 1 mg/mL or 2 mg/mL in a solution such as:

- 5% Dextrose Injection, USP, or
- 0.9% Sodium Chloride Injection, USP

Prepare the diluted QUELICIN solution for single patient use only. Store the diluted QUELICIN solution in a refrigerator [2 °C to 8 °C (36 °F to 46 °F)] and use within 24 hours after preparation. Visually inspect the diluted QUELICIN solution for particulate matter and discoloration prior to administration. Do not administer solutions that are not clear and colorless. Discard any unused portion of the diluted QUELICIN solution.

2.6 Drug Incompatibility

QUELICIN is acidic (pH is between 3.0 and 4.5) and may not be compatible with alkaline solutions having a pH greater than 8.5 (e.g., barbiturate solutions). Therefore, do not mix QUELICIN with alkaline solutions.

3 DOSAGE FORMS AND STRENGTHS

QUELICIN™ (Succinylcholine Chloride Injection, USP) is supplied as a clear, colorless solution as follows:

- 1,000 mg/10 mL (100 mg/mL) in single-dose fliptop vials contains: 100 mg of succinylcholine anhydrous (equivalent to 113.27 mg of Succinylcholine Chloride, USP).
- 200 mg/10 mL (20 mg/mL) in multiple-dose fliptop vials contains: 20 mg of succinylcholine anhydrous (equivalent to 22.65 mg of Succinylcholine Chloride, USP).

4 CONTRAINDICATIONS

QUELICIN is contraindicated:

- in patients with skeletal muscle myopathies [see Warnings and Precautions (5.1)]
- in patients with known hypersensitivity to succinylcholine. Severe anaphylactic reactions to succinylcholine have been reported [see Warnings and Precautions (5.2)]
- after the acute phase of injury following major burns, multiple trauma, extensive denervation of skeletal muscle, or upper motor neuron injury, which may result in severe hyperkalemia and cardiac arrest [see Warnings and Precautions (5.4)]
- in patients with known or suspected genetic susceptibility to malignant hyperthermia [see Warnings and Precautions (5.5), Clinical Pharmacology (12.5)]

5 WARNINGS AND PRECAUTIONS

5.1 Ventricular Dysrhythmias, Cardiac Arrest, and Death From Hyperkalemic Rhabdomyolysis in Pediatric Patients

There have been reports of ventricular dysrhythmias, cardiac arrest, and death secondary to acute rhabdomyolysis with hyperkalemia in apparently healthy pediatric patients who received succinylcholine. Many of these pediatric patients were subsequently found to have a skeletal muscle myopathy such as Duchenne muscular dystrophy whose clinical signs were not obvious.

The syndrome often presented as sudden cardiac arrest within minutes after the administration of succinylcholine. These pediatric patients were usually, but not exclusively, males, and most frequently 8 years of age or younger. There have also been reports in adolescents. There may be no signs or symptoms to alert the practitioner to which patients are at risk. A careful history and physical may identify developmental delays suggestive of a myopathy. A preoperative creatine kinase could identify some but not all patients at risk.

When a healthy-appearing pediatric patient develops cardiac arrest within minutes after administration of QUELICIN, not felt to be due to inadequate ventilation, oxygenation or anesthetic overdose, immediate treatment for hyperkalemia should be instituted. Due to the abrupt onset of this syndrome, routine resuscitative measures are likely to be unsuccessful. Careful monitoring of the electrocardiogram may alert the practitioner to peaked T-waves (an early sign). Administration of intravenous calcium, bicarbonate, and glucose with insulin, with hyperventilation have resulted in successful resuscitation in some of the reported cases. Extraordinary and prolonged resuscitative efforts have been effective in some cases. In addition, in the presence of signs of malignant hyperthermia, appropriate treatment should be initiated concurrently [see Warnings and Precautions (5.5)].

Because it is difficult to identify which patients are at risk, reserve the use of QUELICIN in pediatric patients for emergency intubation or instances where immediate securing of the airway is necessary, e.g., laryngospasm, difficult airway, full stomach, or for intramuscular use when a suitable vein is inaccessible.

5.2 Anaphylaxis

Severe anaphylactic reactions to neuromuscular blocking agents, including succinylcholine, have been reported. These reactions have, in some cases, been life-threatening and fatal. Due to the potential severity of these reactions, the necessary precautions, such as the immediate availability of appropriate emergency treatment, should be taken. Allergic cross-reactivity between neuromuscular blocking agents, both depolarizing and non-depolarizing, has been reported in this class of drugs. Therefore, assess patients for previous anaphylactic reactions to other neuromuscular blocking agents before administering QUELICIN.

5.3 Risk of Death due to Medication Errors

Administration of QUELICIN results in paralysis, which may lead to respiratory arrest and death; this progression may be more likely to occur in a patient for whom it is not intended. Confirm proper selection of intended product and avoid confusion with other injectable solutions that are present in critical care and other clinical settings. If another healthcare provider is administering the product, ensure that the intended dose is clearly labeled and communicated.

5.4 Hyperkalemia

QUELICIN may induce serious cardiac arrhythmias or cardiac arrest due to hyperkalemia in patients with electrolyte abnormalities and those who may have digitalis toxicity.

QUELICIN is contraindicated after the acute phase of injury following major burns, multiple trauma, extensive denervation of skeletal muscle, or upper motor neuron injury [see Contraindications (4)]. The risk of hyperkalemia in these patients increases over time and usually peaks at 7 to 10 days after the injury. The risk is dependent on the extent and location of the injury. The precise time of onset and the duration of the risk period are undetermined.

Patients with chronic abdominal infection, subarachnoid hemorrhage, or conditions causing degeneration of central and peripheral nervous systems are at an increased risk of developing severe hyperkalemia after QUELICIN administration. Consider avoiding use of QUELICIN in these patients or verify the patient's baseline potassium levels are within the normal range prior to QUELICIN administration.

5.5 Malignant Hyperthermia

In susceptible individuals, succinylcholine may trigger malignant hyperthermia, a skeletal muscle hypermetabolic state leading to high oxygen demand. Fatal outcomes of malignant hyperthermia have been reported.

The risk of developing malignant hyperthermia increases with the concomitant administration of succinylcholine and volatile anesthetic agents. QUELICIN can induce malignant hyperthermia in patients with known or suspected susceptibility based on genetic factors or family history, including those with certain inherited ryanodine receptor (RYR1) or dihydropyridine receptor (CACNA1S) variants. [see Contraindications (4), Clinical Pharmacology (12.5)].

Signs consistent with malignant hyperthermia may include hyperthermia, hypoxia, hypercapnia, muscle rigidity (e.g., jaw muscle spasm), tachycardia (e.g., particularly that unresponsive to deepening anesthesia or analgesic medication administration), tachypnea, cyanosis, arrhythmias, hypovolemia, and hemodynamic instability. Skin mottling, coagulopathies, and renal failure may occur later in the course of the hypermetabolic process.

Successful treatment of malignant hyperthermia depends on early recognition of the clinical signs. If malignant hyperthermia is suspected, discontinue all triggering agents (i.e., volatile anesthetic agents and succinylcholine), administer intravenous dantrolene sodium, and initiate supportive therapies. Consult prescribing information for intravenous dantrolene sodium for additional information on patient management. Supportive therapies include administration of supplemental oxygen and respiratory support based on clinical need, maintenance of hemodynamic stability and adequate urinary output, management of fluid and electrolyte balance, correction of acid base derangements, and institution of measures to control rising temperature.

5.6 Bradycardia

Intravenous bolus administration of QUELICIN in pediatric patients (including infants) may result in profound bradycardia or, rarely, asystole. In both adult and pediatric patients the incidence of bradycardia, which may progress to asystole, is higher following a second dose of succinylcholine. The incidence and severity of bradycardia is higher in pediatric patients than adults. Whereas bradycardia is common in pediatric patients after an initial dose of 1.5 mg/kg, bradycardia is seen in adults only after repeated exposure. Pretreatment with anticholinergic agents (e.g., atropine) may reduce the occurrence of bradyarrhythmias.

5.7 Increase in Intraocular Pressure

Succinylcholine causes an increase in intraocular pressure. Avoid QUELICIN in instances in which an increase in intraocular pressure is undesirable (e.g., narrow angle glaucoma, penetrating eye injury) unless the potential benefit of its use outweighs the potential risk.

5.8 Prolonged Neuromuscular Block due to Phase II Block and Tachyphylaxis

When QUELICIN is given over a prolonged period of time, the characteristic depolarization block of the myoneural junction (Phase I block) may change to a block with characteristics superficially resembling a non-depolarizing block (Phase II block). Prolonged respiratory muscle paralysis or weakness may be observed in patients manifesting this transition to Phase II block. Tachyphylaxis occurs with repeated administration [see Clinical Pharmacology (12.2)].

When Phase II block is suspected in cases of prolonged neuromuscular blockade, positive diagnosis should be made by peripheral nerve stimulation, prior to administration of any anticholinesterase drug. Reversal of Phase II block is a medical decision which must be made upon the basis of the patient, clinical pharmacology, and the experience and judgment of the clinician. The presence of Phase II block is indicated by fade of responses to successive stimuli (preferably "train of four"). The use of an anticholinesterase drug such as neostigmine to reverse Phase II block should be accompanied by appropriate doses of an anticholinergic drug to prevent disturbances of cardiac rhythm. After adequate reversal of Phase II block with an anticholinesterase agent, the patient should be continually observed for at least 1 hour for signs of return of muscle relaxation. Reversal should not be attempted unless: (1) a peripheral nerve stimulator is used to determine the presence of Phase II block (since anticholinesterase agents will potentiate succinylcholine-induced Phase I block), and (2) spontaneous recovery of muscle twitch has been observed for at least 20 minutes and has reached a plateau with further recovery proceeding slowly; this delay is to ensure complete hydrolysis of succinylcholine by plasma cholinesterase prior to administration of the anticholinesterase agent. Should the type of block be misdiagnosed, depolarization of the type initially induced by succinylcholine (i.e., Phase I block) will be prolonged by an anticholinesterase agent.

5.9 Risk of Prolonged Neuromuscular Block in Patients with Reduced Plasma Cholinesterase Activity

QUELICIN is not recommended in patients with known reduced plasma cholinesterase (pseudocholinesterase) activity due to the likelihood of prolonged neuromuscular block following administration of QUELICIN in such patients.

Plasma cholinesterase activity may be diminished in the presence of genetic abnormalities of plasma cholinesterase (e.g., patients heterozygous or homozygous for atypical plasma cholinesterase gene), pregnancy, severe liver or kidney disease, malignant tumors, infections, burns, anemia, decompensated heart disease, peptic ulcer, or myxedema. Plasma cholinesterase activity may also be diminished by chronic administration of oral contraceptives, glucocorticoids, or certain monoamine oxidase inhibitors and by irreversible inhibitors of plasma cholinesterase (e.g., organophosphate insecticides, echothiophate, and certain antineoplastic drugs) [see Drug Interactions (7.1)].

Patients homozygous for atypical plasma cholinesterase gene (1 in 2,500 patients) are extremely sensitive to the neuromuscular blocking effect of succinylcholine. If QUELICIN is administered to a patient homozygous for atypical plasma cholinesterase, resulting apnea or prolonged muscle paralysis should be treated with controlled respiration.

5.10 Risk of Additional Trauma in Patients With Fractures or Muscle Spasms

QUELICIN should be employed with caution in patients with fractures or muscle spasm because the initial muscle fasciculations may cause additional trauma. Monitor neuromuscular transmission and the development of fasciculations throughout the use of neuromuscular blocking agents.

5.11 Increase in Intracranial Pressure

QUELICIN may cause a transient increase in intracranial pressure; however, adequate anesthetic induction prior to administration of QUELICIN will minimize this effect.

5.12 Risk of Aspiration due to Increase in Intragastric Pressure

Succinylcholine may increase intragastric pressure, which could result in regurgitation and possible aspiration of stomach contents. Evaluate patients at risk for aspiration and regurgitation. Monitor patients during induction of anesthesia and neuromuscular blockade for clinical signs of vomiting and/or aspiration.

5.13 Prolonged Neuromuscular Block in Patients with Hypokalemia or Hypocalcemia

Neuromuscular blockade may be prolonged in patients with hypokalemia (e.g., after severe vomiting, diarrhea, digitalisation and diuretic therapy) or hypocalcemia (e.g., after massive transfusions). Correct severe electrolyte disturbances when possible. In order to help preclude possible prolongation of neuromuscular block, monitor neuromuscular transmission throughout the use of QUELICIN.

5.14 Risks due to Inadequate Anesthesia

Neuromuscular blockade in the conscious patient can lead to distress. Use QUELICIN in the presence of appropriate sedation or general anesthesia. Monitor patients to ensure that the level of anesthesia is adequate. In emergency situations, however, it may be necessary to administer QUELICIN before unconsciousness is induced.

6 ADVERSE REACTIONS

The following clinically significant adverse reactions are discussed in greater detail in other sections of the labeling:

- Ventricular Dysrhythmias, Cardiac Arrest, and Death from Hyperkalemic Rhabdomyolysis in Pediatric Patients [see Warnings and Precautions (5.1)]
- Anaphylaxis [see Warnings and Precautions (5.2)]
- Hyperkalemia [see Warnings and Precautions (5.4)]
- Malignant Hyperthermia [see Warnings and Precautions (5.5)]
- Bradycardia [see Warnings and Precautions (5.6)]
- Increase in Intraocular Pressure [see Warnings and Precautions (5.7)]
- Prolonged Neuromuscular Block due to Phase II Block and Tachyphylaxis [see Warnings and Precautions (5.8)]

The following adverse reactions associated with the use of succinylcholine were identified in clinical studies or postmarketing reports. Because some of these reactions were reported voluntarily from a population of uncertain size, it is not always possible to reliably estimate their frequency or establish a causal relationship to drug exposure:

Cardiovascular disorders: Cardiac arrest, arrhythmias, bradycardia, tachycardia, hypertension, hypotension

Electrolyte disorders: Hyperkalemia

Eye disorders: Increased intraocular pressure

Gastrointestinal disorders: Excessive salivation

Immune system disorders: Hypersensitivity reactions including anaphylaxis (in some cases life-threatening and fatal)

Musculoskeletal disorders: Malignant hyperthermia, rhabdomyolysis with possible myoglobinuric acute renal failure, muscle fasciculation, jaw rigidity, postoperative muscle pain

Respiratory disorders: Prolonged respiratory depression or apnea

Skin disorders: Rash

7 DRUG INTERACTIONS

7.1 Drugs that May Affect the Neuromuscular Blocking Action of QUELICIN

Drugs that may enhance the neuromuscular blocking action of succinylcholine include: promazine, oxytocin, aprotinin, certain non-penicillin antibiotics, quinidine, β-adrenergic blockers, procainamide, lidocaine, trimethaphan, lithium carbonate, magnesium salts, quinine, chloroquine, isoflurane, desflurane, metoclopramide, and terbutaline.

The neuromuscular blocking effect of succinylcholine may be enhanced by drugs that reduce plasma cholinesterase activity (e.g., chronically administered oral contraceptives, glucocorticoids, or certain monoamine oxidase inhibitors) or by drugs that irreversibly inhibit plasma cholinesterase [see Warnings and Precautions (5.9)].

If other neuromuscular blocking agents are to be used during the same procedure, consider the possibility of a synergistic or antagonistic effect.

8 USE IN SPECIFIC POPULATIONS

8.1 Pregnancy

Risk Summary

Available data from published literature from case reports and case series over decades of use with succinylcholine during pregnancy have not identified a drug-associated risk of major birth defects, miscarriage, or adverse maternal or fetal outcomes. Succinylcholine is used commonly during delivery by caesarean section to provide muscle relaxation. If succinylcholine is used during labor and delivery, there is a risk for prolonged apnea in some pregnant women (see Clinical Considerations). Animal reproduction studies have not been conducted with succinylcholine chloride.

The estimated background risk of major birth defects and miscarriage for the indicated population is unknown. All pregnancies have a background risk of birth defect, loss, or other adverse outcomes. In the U.S. general population, the estimated background risk of major birth defects and miscarriage in clinically recognized pregnancies is 2–4% and 15–20%, respectively.

Clinical Considerations

Maternal Adverse Reactions

Plasma cholinesterase levels are decreased by approximately 24% during pregnancy and for several days postpartum which can prolong the effect of succinylcholine. Therefore, some pregnant patients may experience prolonged apnea.

Fetal/Neonatal Adverse Reactions

Apnea and flaccidity may occur in the newborn after repeated high doses to, or in the presence of atypical plasma cholinesterase in, the mother.

Labor or Delivery

Succinylcholine is commonly used to provide muscle relaxation during delivery by caesarean section. Succinylcholine is known to cross the placental barrier in an amount that is dependent on the concentration gradient between the maternal and fetal circulation.

8.2 Lactation

Risk Summary

There are no data on the presence of succinylcholine or its metabolite in either human or animal milk, the effects on the breastfed infant, or the effects on milk production. The developmental and health benefits of breastfeeding should be considered along with the mother's clinical need for QUELICIN and any potential adverse effects on the breastfed infant from QUELICIN or from the underlying maternal condition.

8.4 Pediatric Use

Safety and effectiveness of succinylcholine chloride have been established in pediatric patient age groups, neonate to adolescent. Because of a risk of ventricular dysrhythmias, cardiac arrest, and death from hyperkalemic rhabdomyolysis in pediatric patients, reserve the use of QUELICIN in pediatric patients for emergency intubation or instances where immediate securing of the airway is necessary, e.g., laryngospasm, difficult airway, full stomach, or for intramuscular use when a suitable vein is inaccessible [see Warnings and Precautions (5.1)].

Intravenous bolus administration of QUELICIN in pediatric patients (including infants) may result in profound bradycardia or, rarely, asystole. The incidence and severity of bradycardia is higher in pediatric patients than adults [see Warnings and Precautions (5.6)].

The effective dose of QUELICIN in pediatric patients may be higher than that predicted by body weight dosing alone [see Dosage and Administration (2.3)].

8.5 Geriatric Use

Clinical studies of QUELICIN did not include sufficient numbers of subjects aged 65 years and over to determine whether they respond differently from younger subjects. Other reported clinical experience has not identified differences in responses between the elderly and younger patients.

In general, dose selection for an elderly patient should be cautious, usually starting at the low end of the dosing range, reflecting the greater frequency of decreased hepatic, renal, or cardiac function, and of concomitant disease or other drug therapy.

10 OVERDOSAGE

Overdosage with QUELICIN may result in neuromuscular block beyond the time needed for surgery and anesthesia. This may be manifested by skeletal muscle weakness, decreased respiratory reserve, low tidal volume, or apnea. The primary treatment is maintenance of a patent airway and respiratory support until recovery of normal respiration is assured. Depending on the dose and duration of QUELICIN administration, the characteristic depolarizing neuromuscular block (Phase I) may change to a block with characteristics superficially resembling a non-depolarizing block (Phase II) [see Warnings and Precautions (5.8)].

11 DESCRIPTION

QUELICIN (Succinylcholine Chloride Injection, USP) is a sterile, nonpyrogenic solution to be used as a short-acting, depolarizing neuromuscular blocker for intravenous or intramuscular use. QUELICIN contains succinylcholine chloride as the active pharmaceutical ingredient.

Succinylcholine Chloride, USP is chemically designated C14H30Cl2N2O4 and its molecular weight is 361.31. The chemical name of succinylcholine chloride is ethanaminium, 2,2'-[(1,4-dioxo-1,4 butanediyl)bis(oxy)]bis[N,N,N-trimethyl-], dichloride. Succinylcholine chloride is a diquaternary base consisting of the dichloride salt of the dicholine ester of succinic acid. It is a white, odorless, slightly bitter powder, very soluble in water. It has the following structural formula:

QUELICIN 1,000 mg/10 mL (100 mg/mL) is intended for single-dose administration and contains no preservative. Each 1 mL of QUELICIN 1,000 mg/10 mL (100 mg/mL) single-dose fliptop vials contains: 100 mg of succinylcholine anhydrous (equivalent to 113.27 mg of Succinylcholine Chloride, USP), and sodium hydroxide and hydrochloric acid as pH adjusters in water for injection. The pH of the solution is between 3.0 and 4.5, with an osmolarity of 0.830 mOsm/mL (calc.).

QUELICIN 200 mg/10 mL (20 mg/mL) is intended for multiple-dose administration and contains preservative. Each 1 mL of QUELICIN 200 mg/10 mL (20 mg/mL) multiple-dose fliptop vials contains: 20 mg of succinylcholine anhydrous (equivalent to 22.65 mg of Succinylcholine Chloride, USP), 1.8 mg of methylparaben and 0.2 mg of propylparaben as preservatives, 4.65 mg of sodium chloride as iso-osmotic agent, and sodium hydroxide and hydrochloric acid as pH adjusters in water for injection. The pH of the solution is between 3.0 and 4.5, with an osmolarity of 0.338 mOsm/mL (calc.).

12 CLINICAL PHARMACOLOGY

12.1 Mechanism of Action

Succinylcholine is a depolarizing neuromuscular blocker. As does acetylcholine, it combines with the cholinergic receptors of the motor end plate to produce depolarization. This depolarization may be observed as fasciculations. Subsequent neuromuscular transmission is inhibited so long as adequate concentration of succinylcholine remains at the receptor site. Onset of flaccid paralysis is rapid (less than one minute after intravenous administration), and with single administration lasts approximately 4 to 6 minutes.

The paralysis following administration of succinylcholine is progressive, with differing sensitivities of different muscles. This initially involves consecutively the levator muscles of the face, muscles of the glottis and finally the intercostals and the diaphragm and all other skeletal muscles.

12.2 Pharmacodynamics

Depending on the dose and duration of succinylcholine administration, the characteristic depolarizing neuromuscular block (Phase I block) may change to a block with characteristics superficially resembling a non-depolarizing block (Phase II block). This may be associated with prolonged respiratory muscle paralysis or weakness in patients who manifest the transition to Phase II block. Tachyphylaxis occurs with repeated administration [see Warnings and Precautions (5.8)]. The transition from Phase I to Phase II block has been reported in 7 of 7 patients studied under halothane anesthesia after an accumulated dose of 2 to 4 mg/kg succinylcholine (administered in repeated, divided doses). The onset of Phase II block coincided with the onset of tachyphylaxis and prolongation of spontaneous recovery. In another study, using balanced anesthesia (N2O/O2/narcotic-thiopental) and succinylcholine infusion, the transition was less abrupt, with great individual variability in the dose of succinylcholine required to produce Phase II block. Of 32 patients studied, 24 developed Phase II block. Tachyphylaxis was not associated with the transition to Phase II block, and 50% of the patients who developed Phase II block experienced prolonged recovery [see Warnings and Precautions (5.8)].

Succinylcholine has no direct effect on the myocardium. Succinylcholine stimulates both autonomic ganglia and muscarinic receptors which may cause changes in cardiac rhythm, including cardiac arrest. Changes in rhythm, including cardiac arrest, may also result from vagal stimulation, which may occur during surgical procedures, or from hyperkalemia, particularly in pediatric patients [see Warnings and Precautions (5.1, 5.4, 5.6), Use in Specific Populations (8.4)]. These effects are enhanced by halogenated anesthetics.

Succinylcholine causes an increase in intraocular pressure immediately after its injection and during the fasciculation phase, and increases which may persist after onset of complete paralysis [see Warnings and Precautions (5.7)].

Succinylcholine may cause increases in intracranial pressure immediately after its injection and during the fasciculation phase [see Warnings and Precautions (5.11)].

As with other neuromuscular blocking agents, the potential for releasing histamine is present following succinylcholine administration. Signs and symptoms of histamine-mediated release such as flushing, hypotension and bronchoconstriction are, however, uncommon with normal clinical usage.

Succinylcholine has no effect on consciousness, pain threshold or cerebration [see Warnings and Precautions (5.14)].

Succinylcholine has no direct action on the uterus or other smooth muscle structures.

12.3 Pharmacokinetics

Elimination

Succinylcholine levels were reported to be below the detection limit of 2 µg/mL after 2.5 minutes of an intravenous bolus dose of 1 or 2 mg/kg in 14 anesthetized patients.

Metabolism

Succinylcholine is rapidly hydrolyzed by plasma cholinesterase to succinylmonocholine (which possesses clinically insignificant depolarizing muscle relaxant properties) and then more slowly to succinic acid and choline.

Excretion

About 10% of the drug is excreted unchanged in the urine.

Specific Populations

Pediatric Patients

Due to the relatively large volume of distribution in the pediatric patient versus the adult patient, the effective dose of QUELICIN in pediatric patients may be higher than that predicted by body weight dosing alone [see Dosage and Administration (2.3)].

12.5 Pharmacogenomics

RYR1 and CACNA1S are polymorphic genes and multiple pathogenic variants have been associated with malignant hyperthermia susceptibility (MHS) in patients receiving succinylcholine, including QUELICIN. Case reports as well as ex-vivo studies have identified multiple variants in RYR1 and CACNA1S associated with MHS. Variant pathogenicity should be assessed based on prior clinical experience, functional studies, prevalence information, or other evidence [see Contraindications (4), Warnings and Precautions (5.5)].

13 NONCLINICAL TOXICOLOGY

13.1 Carcinogenesis, Mutagenesis, Impairment of Fertility

Carcinogenesis

There have been no long-term studies performed in animals to evaluate carcinogenic potential of succinylcholine.

Mutagenesis

Adequate studies have not been completed to evaluate the genotoxic potential of succinylcholine.

Impairment of Fertility

There are no studies to evaluate the potential impact of succinylcholine on fertility.

16 HOW SUPPLIED/STORAGE AND HANDLING

QUELICIN™ (Succinylcholine Chloride Injection, USP) is supplied as a clear, colorless solution in the following concentrations and packages:

Unit of Sale | Concentration
NDC 0409-6970-10 Tray containing 25 Single-dose Fliptop Vials | 1,000 mg/10 mL (100 mg/mL)
NDC 0409-6629-02 Tray containing 25 Multiple-dose Fliptop Vials | 200 mg/10 mL (20 mg/mL)

Refrigeration of undiluted QUELICIN will assure full potency until expiration date.

Single-dose Fliptop Vials: Discard unused portion.

STORAGE AND HANDLING

Store in refrigerator 2 °C to 8 °C (36 °F to 46 °F). The multiple-dose vials are stable for up to 14 days at room temperature without significant loss of potency.

Distributed by Hospira, Inc., Lake Forest, IL 60045 USA

LAB-1246-6.0

This product's labeling may have been updated. For the most recent Prescribing Information, please visit www.pfizer.com.

For Medical Information about QUELICIN, please visit www.pfizermedinfo.com or call 1-800-438-1985.

PRINCIPAL DISPLAY PANEL - 20 mg/mL Vial Label

10 mL

NDC 0409-6629-12

SUCCINYLCHOLINE
CHLORIDE INJECTION, USP

200 mg/10 mL (20 mg/mL)

WARNING: Paralyzing Agent

QUELICIN™

WARNING: Paralyzing Agent. Causes Respiratory Arrest.
Facilities must be immediately available for artificial respiration

PRINCIPAL DISPLAY PANEL - 20 mg/mL Vial Tray

10 mL Multiple-dose

NDC 0409-6629-02
Contains 25 of NDC 0409-6629-12

SUCCINYLCHOLINE
CHLORIDE INJECTION, USP

Rx only

QUELICIN™ 200 mg/10 mL (20 mg/mL)

WARNING: Paralyzing Agent

Store in refrigerator 2° to 8°C (36° to 46°F).

Hospira

PRINCIPAL DISPLAY PANEL - 100 mg/mL Vial Label

10 mL Single-dose

SUCCINYLCHOLINE
CHLORIDE INJECTION, USP

1,000 mg/10 mL (100 mg/mL)
WARNING: Paralyzing Agent

QUELICIN®

WARNING: Paralyzing Agent. Causes Respiratory Arrest.
Facilities must be immediately available for artificial respiration

Hospira, Inc., Lake Forest, IL 60045 USA

PRINCIPAL DISPLAY PANEL - 100 mg/mL Vial Tray

10 mL Single Dose Fliptop Vial-Discard Unused Portion
25 Units/NDC 0409-6970-10

SUCCINYLCHOLINE
CHLORIDE INJECTION, USP

QUELICIN® 1,000 mg/10 mL (100 mg/mL)

CAUTION: MUST BE DILUTED.
FOR INTRAVENOUS USE.

Store in refrigerator 2° to 8°C (36° to 46°F).

WARNING: Paralyzing Agent
Rx only

Hospira